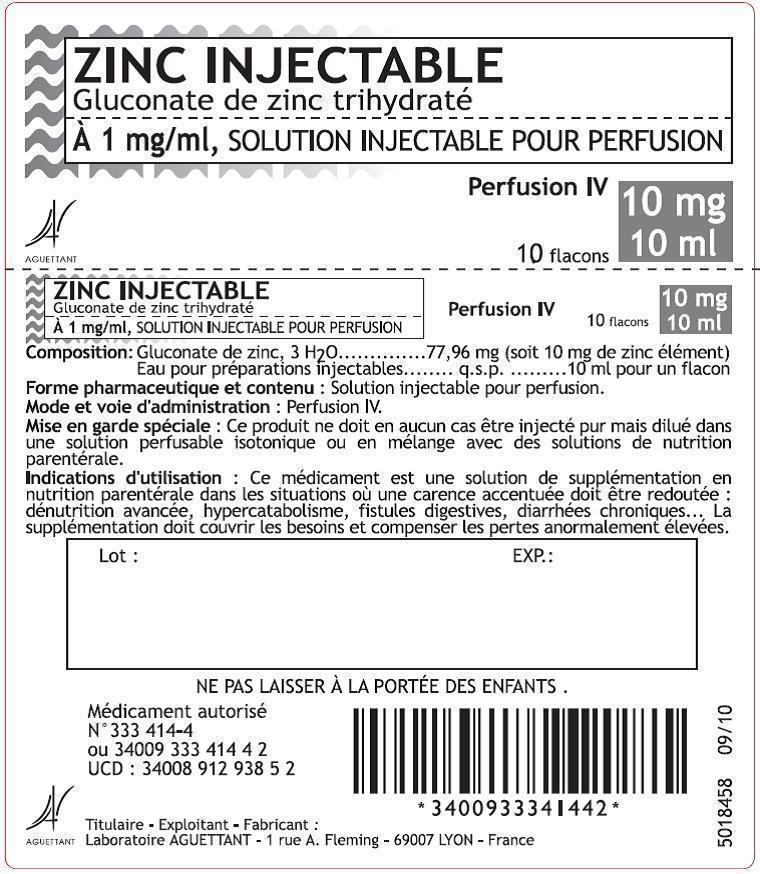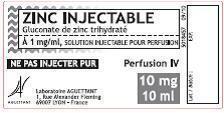 DRUG LABEL: ZINC INJECTABLE A 1mg/ml, solution injectable pour perfusion
NDC: 60710-001 | Form: INJECTION, SOLUTION
Manufacturer: Laboratoire Aguettant
Category: prescription | Type: HUMAN PRESCRIPTION DRUG LABEL
Date: 20180809

ACTIVE INGREDIENTS: ZINC GLUCONATE TRIHYDRATE 1 mg/1 mL
INACTIVE INGREDIENTS: WATER

ZINC INJECTABLE A 1mg/ml, solution injectable pour perfusion

Dear Healthcare Provider Letter

Laboratoire AGUETTANT 1 Rue Alexander Fleming 69007 LYON - FRANCE

IMPORTANT DRUG INFORMATION

ZINC INJECTION AVAILABILITY

July 23, 2013

Subject: Temporary importation of Zinc injectable 1 mg/ml (zinc gluconate trihydrate) solution for infusion (equivalent to elemental zinc 1 mg/mL)

Dear Healthcare Professional,

Due to the current critical shortage of zinc injection drug products in the United States (U.S.), Laboratoire Aguettant (Aguettant) is coordinating with the Food and Drug Administration (FDA) to increase the availability of these products. Aguettant has initiated temporary importation into the U.S., through its U.S. distributor Baxter Healthcare Corporation, the non-FDA-approved zinc-containing drug, Zinc injectable 1 mg/mL (zinc gluconate trihydrate) solution for infusion (equivalent to elemental zinc 1 mg/mL): Lot T-7506C, expiration date 02-2015, and Lot T-7519C, expiration date 03-2015.This product is marketed in France, and is manufactured for Aguettant at a FDA-inspected facility in France that is in compliance with Good Manufacturing Practices (GMP) regulations enforced in Europe.

At this time, FDA's regulatory discretion for the importation and distribution of Aguettant's Zinc injectable 1 mg/mL (zinc gluconate trihydrate) solution for infusion (equivalent to elemental zinc 1 mg/mL) is limited to Aguettant and its distributor Baxter Healthcare Corporation during the critical shortage of zinc injection. Importation and distributionof this product in the United States byany entity other than Aguettant and its distributor Baxter Healthcare Corporation is outside the scope of FDA's regulatory discretion, and FDA has not approved Aguettant's Zinc injectable product in the U.S.

Effective immediately, and during this temporary period, Aguettant will offer the following presentation of zinc injection:

Zinc Injectable

(zinc gluconate trihydrate)

1 mg/mL, solution for infusion

10 mL glass vials

Authorization# 333 414-4 (France)

Box of 10 vials

The vial and carton labels will display the original French product labels as marketed inFrance. At the end of this letter is a product comparison table with the French prescribing information translated into English, as well as images of the French labels with their English translation for your reference.

Zinc injectable 1 mg/mL (zinc gluconate trihydrate) solution for infusion is meant to be used the same way as the U.S. marketed drugs, and provides 1 mg/mL of elemental zinc. Each vial is single use only and must be diluted prior to infusion. Please discard each vial after single use.

There are some key differences in labeling between the FDA-approved zinc injection drug product and Aguettant's zinc injectable 1 mg/mL (zinc gluconate trihydrate) solution for infusion (please see also the product comparison tables attached).

- Zinc injectable 1 mg/mL solution for infusion (equivalent to elemental zinc 1 mg/mL) contains zinc gluconate trihydrate as the active substance, which is a different salt than those used in other zinc drugs for injection, i.e. zinc chloride and zinc sulfate. Also, note that our manufacturer of zinc gluconate trihydrate complies with the U.S. Pharmacopoeia monograph for zinc gluconate trihydrate. We consider this formulation an appropriate alternative to the FDA-approved zinc injection drug product when used as explained below.
- The composition in active substance is equivalent to one milligram of elemental zinc per milliliter of solution. The only excipient is water for injections, and the pH of the drug is comprised between 5.5 and 7.0.
- No specific precautions are required for the storage of Zinc injectable 1 mg/mL (zinc gluconate trihydrate) solution for infusion. As with your usual zinc injection drug products, you may store this at controlled room temperature 20°C to 25°C (68°F to 77°F).

Zinc injectable 1 mg/mL (zinc gluconate trihydrate) solution for infusion is available only by prescription in theU.S.

Please refer to the package insert for the FDA-approved zinc injection drug product for full prescribing information and follow the instructions presented in the FDA-approved package insert for dosing and use in pregnancy recommendations. Please note the difference in the maximum potential aluminum content (higher in the foreign product).

- Zinc injectable 1 mg/mL (zinc gluconate trihydrate), solution for infusion is meant to be used by parenteral administration (infusion), only after dilution in an isotonic solution or in a mixture for parenteral nutrition.
- Dosing instructions for Zinc injectable 1 mg/mL (zinc gluconate trihydrate), solution for infusion differ from dosing instructions for the FDA-approved zinc injection drug product. We recommend that you follow the labeling instructions for the FDA-approved zinc injection drug product.
- Instructions regarding use in pregnancy for Zinc injectable 1 mg/mL (zinc gluconate trihydrate), solution for infusion differ from dosing instructions for the FDA-approved zinc injection drug product. We recommend that you follow the labeling instructions for the FDA-approved zinc injection drug product.
- Maximum potential aluminum content for Zinc injectable 1 mg/mL (zinc gluconate trihydrate), solution for infusion is higher than that for the FDA-approved zinc injection drug product. Consider risks of aluminum toxicity against benefit of zinc supplementation when prescribing Zinc injectable 1 mg/mL (zinc gluconate trihydrate), solution for infusion.

The aluminum content of Lot T-7506C and Lot T-7519C is each no more than 100 mcg/L at the time of this import. Aluminum testing is not a requirement for registration of this product inFrance. However in support of FDA's regulatory discretion for temporary importation, testing was performed perU.S.regulation 21 CFR 201.323. The aluminum content for lots at expiry was found to be no higher than 350 mcg/L.

The barcodemay not registeraccurately on the U.S. scanning systems. Institutions should manually input the product into their systems and confirm that barcode systems do not provide incorrect information when the product is scanned. Alternative procedures should be followed to assure that the correct drug product is being used and administered to individual patients.

To place an order, or if you have any questions about the information contained in this letter or the use of Zinc injectable 1 mg/mL (zinc gluconate trihydrate) solution for infusion, please call Baxter's Center for Service at 1-888-229-0001, available from 7:00 am to 6:00 pm Central Standard Time, or email CFS_Customer_Service@baxter.com.

We encourage health care providers to report any adverse events and medication errors that occur while using this product, as for any other drug. To report adverse events associated with Zinc injectable 1 mg/mL (zinc gluconate trihydrate) solution for infusion, please call Baxter Healthcare Surveillance at 1-866-888-2472 (Monday – Friday 9:00 am to 5:00 pm Central Standard Time), or fax at 1-800-759-1801 (24 hrs/day, 7 days/week).

Adverse events that may be related to the use of this product may also be reported to FDA's MedWatch Adverse Event Reporting Program either online, by regular mail or by fax:

- Online: http://www.fda.gov/medwatch/report.htm
- Regular mail: Use postage paid FDA form 3500 available at :

http://www.fda.gov/medwatch/getforms.htm

Mail to MedWatch FDA,5600 Fishers Lane,Rockville,MD20852-9787

- Fax: 1-800-FDA-0178

We remain at your disposal to answer the questions you might have about our product, and provide more information if needed.

Thank you for your understanding,

Eric ROUGEMOND, MD CEO of Laboratoire Aguettant

Product comparison tables

 | ZINC 1 mg/ml zinc chloride injection, USP; FDA-approved zinc injection drug product | Zinc injectable 1 mg/ml, solution for infusion; (translated into English); Laboratoire Aguettant
Composition
Active ingredient | Zinc Chloride, USP | Zinc Gluconate, USP
Strength | 2.09 mg/mL zinc chloride equivalent to 1 mg/mL elemental zinc | 7.80 mg/mL zinc gluconate equivalent to 1 mg/mL elemental zinc
Inactive ingredients | Sodium chloride 9 mg/mL; Hydrochloric acid or sodium hydroxide for pH adjustment | Water for injections
Content in aluminum | Not more than 150 mcg/L | Not more than 1500 mcg/L; (not stated on the insert)
Physiochemical parameters
pH | 2.0 (1.5 to 2.5) | 5.5 to 7.0 (not stated on the insert)
Osmolarity | 0.354 mOsmol/mL (calc.) | 0.30 to 0.35 mOsmol/mL; (not stated on the insert)
Description | Sterile, non-pyrogenic solution intended for use as an additive to intravenous solutions for total parenteral nutrition (TPN).; The solution contains no bacteriostat, antimicrobial agent or added buffer. | Solution for infusion.; Supplementation solution for prolonged parenteral nutrition and for prevention of severe zinc deficiency.; Sterile solution; (not stated on the insert); The solution contains no bacteriostat, antimicrobial agent or added buffer.; (not stated on the insert)
How supplied | 10 mL plastic vials | 10 mL glass vials; pack of 10 vials
Storage conditions | Store at 20 to25°C(68 to77°F). [See USP Controlled Room Temperature.] | No special precautions for storage.
Country-specific information |  | Marketing Authorization Number: 333 414-4
Expiration date format |  | MM/YYYY
Drug status | Rx only | Non-prescription drug
Authorization holder |  | Laboratoire AGUETTANT; 1, rue Alexander Fleming; 69007 LYON; FRANCE

Comparison of prescribing information
Clinical pharmacology; 5.1 Pharmacodynamic properties; 5.2 Pharmacokinetic properties; 5.3 Preclinical safety data | Zinc is an essential nutritional requirement and serves as a cofactor for more than 70 different enzymes including carbonic anhydrase, alkaline phosphatase, lactic dehydrogenase, and both RNA and DNA polymerase. Zinc facilitates wound healing, helps maintain normal growth rates, normal skin hydration, and the senses of taste and smell.; Zinc resides in muscle, bone, skin, kidney, liver, pancreas, retina, prostate and particularly in the red and white blood cells. Zinc binds to plasma albumin, a2-macroglobulin, and some plasma amino acids including histidine, cysteine, threonine, glycine, and asparagine.; Ingested zinc is excreted mainly in the stool (approximately 90%), and to a lesser extent in the urine and in perspiration.; Providing zinc helps prevent development of deficiency symptoms such as: Parakeratosis, hypogeusia, anorexia, dysosmia, geophagia, hypogonadism, growth retardation and hepatosplenomegaly.; The initial manifestations of hypozincemia in TPN are diarrhea, apathy and depression. At plasma levels below 20 mcg zinc/100 mL dermatitis followed by alopecia has been reported for TPN patients. Normal zinc plasma levels are 100 ± 12 mcg/100 mL. | 5.1 Pharmacodynamic properties; INTRAVENOUS SOLUTIONS; (B: BLOOD AND BLOOD FORMING ORGANS); Zinc is an essential component of at least 120 metalloenzymes including carbonic anhydrases, alkaline phosphatases, carboxypeptidases, oxidoreductases, transferases, ligases, hydrolases, isomerases and alcohol dehydrogenases.; Zinc also has an important role in the synthesis of nucleic acids (DNA and RNA) and in the regulation of RNA catabolism.; Zinc is involved in the transformation of T-lymphocytes and might be involved in the synthesis of insulin.; Hence, zinc participates in the metabolism of carbohydrates, lipids and proteins.; Zinc is indispensable for the growth of premature and full term infants and children.; 5.2 Pharmacokinetic properties; Not available.; 5.3 Preclinical safety data; Not available.
Indications and usage; 4.1 Therapeutic indications | Zinc 1 mg/mL (Zinc Chloride Injection, USP) is indicated for use as a supplement to intravenous solutions given for TPN.; Administration helps to maintain zinc serum levels and to prevent depletion of endogenous stores, and subsequent deficiency symptoms. | Supplementation solution for prolonged parenteral nutrition and for prevention of severe zinc deficiency in conditions such as (but not limited to) severe denutrition, hypercatabolism, digestive fistula, chronic diarrhea.; The supplementation scheme must cover the daily needs (3 to 4 mg zinc per day for adults) and compensate for abnormally high losses (up to 15 mg per day).
Contraindications; 4.3 Contraindications | None known. | Hypersensitivity to any of the ingredients.
Warnings | Direct intramuscular or intravenous injection of Zinc 1 mg/mL (Zinc Chloride Injection, USP) is contraindicated as the acidic pH of the solution (2) may cause considerable tissue irritation.; Severe kidney disease may make it necessary to reduce or omit chromium and zinc doses because these elements are primarily eliminated in the urine.; WARNING: This product contains aluminum that may be toxic. Aluminum may reach toxic levels with prolonged parenteral administration if kidney function is impaired. Premature neonates are particularly at risk because their kidneys are immature, and they require large amounts of calcium and phosphate solutions, which contain aluminum.; Research indicates that patients with impaired kidney function, including premature neonates, who receive parenteral levels of aluminum at greater than 4 to 5 mcg/kg/day accumulate aluminum at levels associated with central nervous system and bone toxicity.; Tissue loading may occur at even lower rates of administration. | 4.4 Special warnings and precautions for use; Warning; This product must never be injected as is, but diluted in a solution for infusion.; 4.5 Interaction with other medicinal products and other forms of interaction; In complex parenteral nutrition protocols, special precaution is required to avoid incompatibilities among the added medications.
Precautions; 4.6 Pregnancy and lactation; 4.7 Effects on ability to drive and use machines; 6.2 Incompatibilities | General; Do not use unless the solution is clear and the seal is intact.; Zinc 1 mg/mL (Zinc Chloride Injection, USP) should only be used in conjunction with a pharmacy directed admixture program using aseptic technique in a laminar flow environment; it should be used promptly and in a single operation without any repeated penetrations. Solution contains no preservatives; discard unused portion immediately after admixture procedure is completed.; Zinc should not be given undiluted by direct injection into a peripheral vein because of the likelihood of infusion phlebitis and the potential for increased excretory loss of zinc from a bolus injection. Administration of zinc in the absence of copper may cause a decrease in serum copper levels.; Laboratory Tests; Periodic determinations of serum copper as well as zinc are suggested as a guideline for subsequent zinc administration.; Carcinogenesis, Mutagenesis, and Impairment of Fertility; Long-term animal studies to evaluate the carcinogenic potential of Zinc 1 mg/mL (Zinc Chloride Injection, USP) have not been performed, nor have studies been done to assess mutagenesis or impairment of fertility.; Nursing Mothers; It is not known whether this drug is excreted in human milk. Because many drugs are excreted in human milk, caution should be exercised when Zinc 1 mg/mL (Zinc Chloride Injection, USP) is administered to a nursing woman.; Pediatric Use; See DOSAGE and ADMINISTRATION section.; Pregnancy Category C. Animal reproduction studies have not been conducted with zinc chloride. It is also not known whether zinc chloride can cause fetal harm when administered to a pregnant woman or can affect reproduction capacity. Zinc chloride should be given to a pregnant woman only if clearly needed.; Geriatric Use; An evaluation of current literature revealed no clinical experience identifying differences in response between elderly and younger patients. In general, dose selection for an elderly patient should be cautious, usually starting at the low end of the dosing range, reflecting the greater frequency of decreased hepatic, renal, or cardiac function, and of concomitant disease or other drug therapy. | 4.6 Pregnancy and lactation; Based on available data, it is possible to use this product for pregnant or breast-feeding women.; 4.7 Effects on ability to drive and use machines; Not relevant.; 6.2 Incompatibilities; In the absence of compatibility studies, this medicinal product must not be mixed with other medicinal products.
Adverse reactions; 4.8 Undesirable effects | None known. | Adverse effects are observed with high dosages (see section 4.9).
Drug abuse and dependence; (No equivalent section) | None known.
Overdosage; 4.9 Overdose | Single intravenous doses of 1 to 2 mg zinc/kg body weight have been given to adult leukemic patients without toxic manifestations.; However, acute toxicity was reported in an adult when 10 mg zinc was infused over a period of one hour on each of four consecutive days. Profuse sweating, decreased level of consciousness, blurred vision, tachycardia (140/min), and marked hypothermia (94.2° F) on the fourth day were accompanied by a serum zinc concentration of 207 mcg/dl. Symptoms abated within three hours.; Hyperamylasemia may be a sign of impending zinc overdosage; patients receiving an inadvertent overdose (25 mg zinc/liter of TPN solution, equivalent to 50 to 70 mg zinc/day) developed hyperamylasemia (557 to 1850 Klein units; normal: 130 to 310).; Death resulted from an overdosage in which 1683 mg zinc was delivered intravenously over the course of 60 hours to a 72 year old patient.; Symptoms of zinc toxicity included hypotension (80/40 mm Hg), pulmonary edema, diarrhea, vomiting, jaundice, and oliguria, with a serum zinc level of 4184 mcg/dl.; Calcium supplements may confer a protective effect against zinc toxicity. | No overdose cases were reported with ZINC INJECTABLE 1mg/ml, solution for infusion.; However, overdose cases by intravenous injection of zinc were reported with manifestations of acute toxicity such as profuse sweating, blurred vision, decreased level of consciousness, hypothermia, tachycardia, jaundice and pulmonary edema. Hyperamylasemia may be a sign of impending zinc overdosage.; Calcium supplementation may confer a protective effect.
Dosage and administration; 4.2 Posology and method of administration; 6.6 Special precautions for disposal and other handling | Zinc 1 mg/mL (Zinc Chloride Injection, USP) contains 1 mg zinc/mL and is administered intravenously only after dilution. The additive should be diluted prior to administration in a volume of fluid not less than 100 mL. For the metabolically stable adult receiving TPN, the suggested intravenous dosage is 2.5 to 4 mg zinc/day (2.5 to 4 mL/day). An additional 2 mg zinc/day (2 mL/day) is suggested for acute catabolic states. For the stable adult with fluid loss from the small bowel, an additional 12.2 mg zinc/liter of small bowel fluid lost (12.2 mL/liter of small bowel fluid lost), or an additional 17.1 mg zinc/kg of stool or ileostomy output (17.1 mL/kg of stool or ileostomy output) is recommended. Frequent monitoring of zinc blood levels is suggested for patients receiving more than the usual maintenance dosage level of zinc.; For full term infants and children up to 5 years of age, 100 mcg zinc/kg/day (0.1 mL/kg/day) is recommended. For premature infants (birth weight less than 1500 g) up to 3 kg in body weight, 300 mcg zinc/kg/day (0.3 mL/kg/day) is suggested.; Parenteral drug products should be inspected visually for particulate matter and discoloration prior to administration, whenever solution and container permit. See PRECAUTIONS. | 4.2 Posology and method of administration; Each mL contains 1 mg of elemental zinc.; The dosage must be adapted to each patient, taking into account losses and zinc status.; The solution is a supplementation additive for parenteral nutrition intended to be used in mixtures for parenteral nutrition or diluted in isotonic solutions.; Recommended daily intakes by intravenous route are the following:; - In pediatric patients:; - Premature infants: 0.3 to 0.35 mg zinc/kg/day,; - Full term infants: 0.1 to 0.2 mg zinc/kg/day,; - Children: 5 mg zinc/day.; - In adults: 3 to 15 mg zinc/day.; 6.6 Special precautions for disposal and other handling; No special precautions.

TRANSLATION OF FRENCH VIAL AND CARTON LABELS
 | Zinc injectable 1 mg/ml, solution for infusion; Product will be distributed with the; original French labels; Laboratoire Aguettant | Zinc injectable 1 mg/ml, solution for infusion; English translation – for information only; Product will be distributed with the; original French labels; Laboratoire Aguettant
Carton Label |  | (not stated on the label): Please refer to the package insert for the FDA-approved zinc injection drug product (zinc chloride injection, 1 mg/mL) for full prescribing information.
Vial Label |  | (not stated on the label):Equivalent to elemental zinc 1 mg/mL.